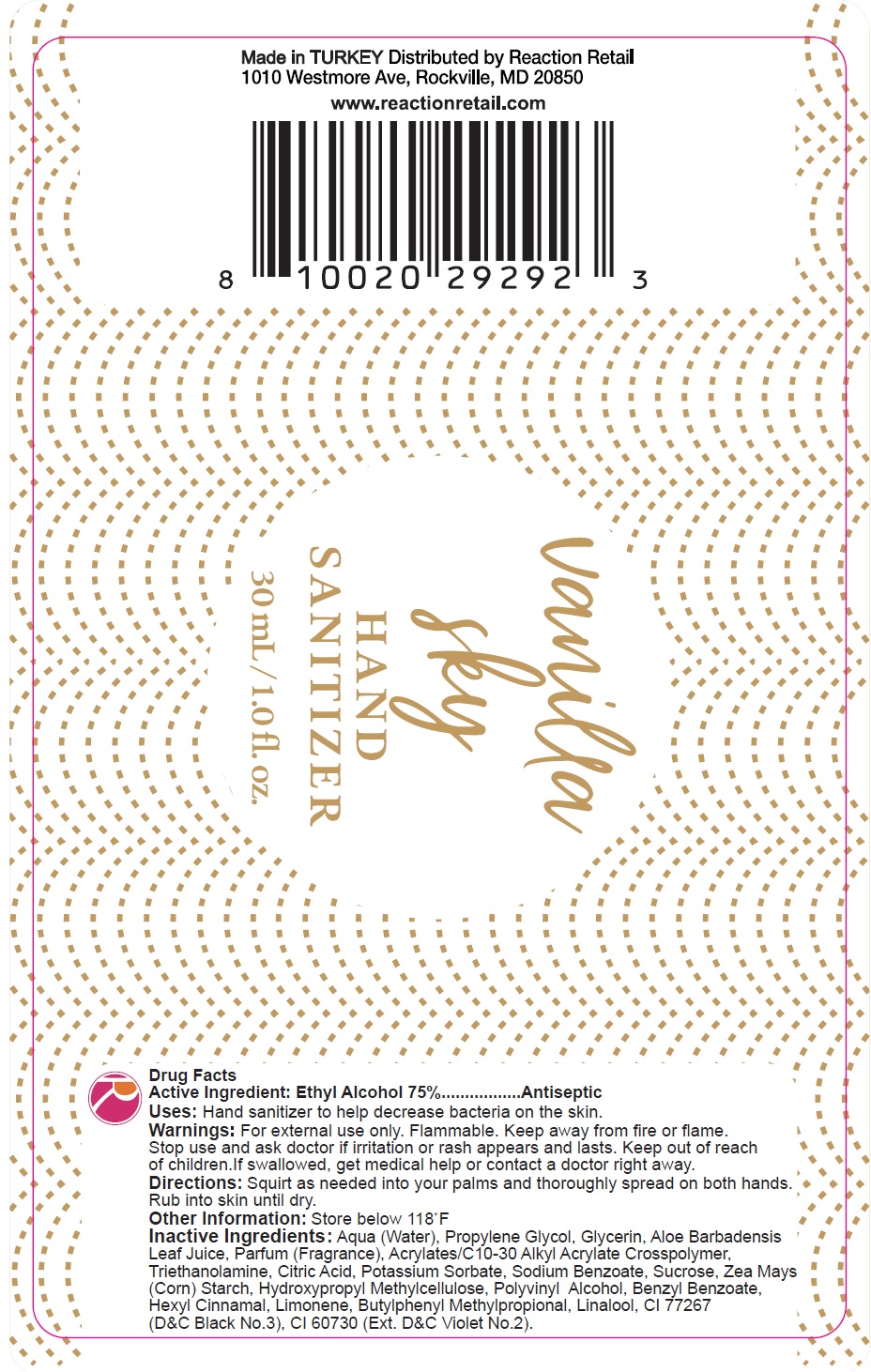 DRUG LABEL: Vanilla Sky Hand Sanitizer
NDC: 80026-004 | Form: GEL
Manufacturer: Reaction Retail, LLC
Category: otc | Type: HUMAN OTC DRUG LABEL
Date: 20200817

ACTIVE INGREDIENTS: ALCOHOL 0.75 mL/1 mL
INACTIVE INGREDIENTS: WATER; PROPYLENE GLYCOL; GLYCERIN; ALOE VERA LEAF; CARBOMER INTERPOLYMER TYPE A (ALLYL SUCROSE CROSSLINKED); TROLAMINE; CITRIC ACID MONOHYDRATE; POTASSIUM SORBATE; SODIUM BENZOATE; SUCROSE; CORN; HYPROMELLOSE, UNSPECIFIED; POLYVINYL ALCOHOL, UNSPECIFIED; BENZYL BENZOATE; .ALPHA.-HEXYLCINNAMALDEHYDE; LIMONENE, (+)-; BUTYLPHENYL METHYLPROPIONAL; LINALOOL, (+/-)-; D&C BLACK NO. 2; EXT. D&C VIOLET NO. 2

Vanilla Sky Hand Sanitizer

Active Ingredient:

Ethyl Alcohol 75%

PURPOSE

Antiseptic

Uses:

Hand sanitizer to help decrease bacteria on the skin.

Warnings:

For external use only. Flammable. Keep away from fire or flame.

Stop use and ask doctor if

irritation or rash appears and lasts.

Keep out of reach of children.

If swallowed, get medical help or contact a doctor right away.

Directions:

Squirt as needed into your palms and thoroughly spread on both hands. Rub into skin until dry.

Other Information:

Store below 118 F

Inactive Ingredients:

Aqua (Water), Propylene Glycol, Glycerin, Aloe Barbadensis Leaf Juice, Parfum (Fragrance), Acrylates/C10-30 Alkyl Acrylate Crosspolymer, Triethanolamine, Citric Acid, Potassium Sorbate, Sodium Benzoate, Sucrose, Zea Mays (Corn) Starch, Hydroxypropyl Methylcellulose, Polyvinyl Alcohol, Benzyl Benzoate, Hexyl Cinnamal, Limonene, Butylphenyl Methylpropional, Linalool, CI 77267 (D&C Black No. 3), CI 60730 (Ext. D&C Violet No.2).